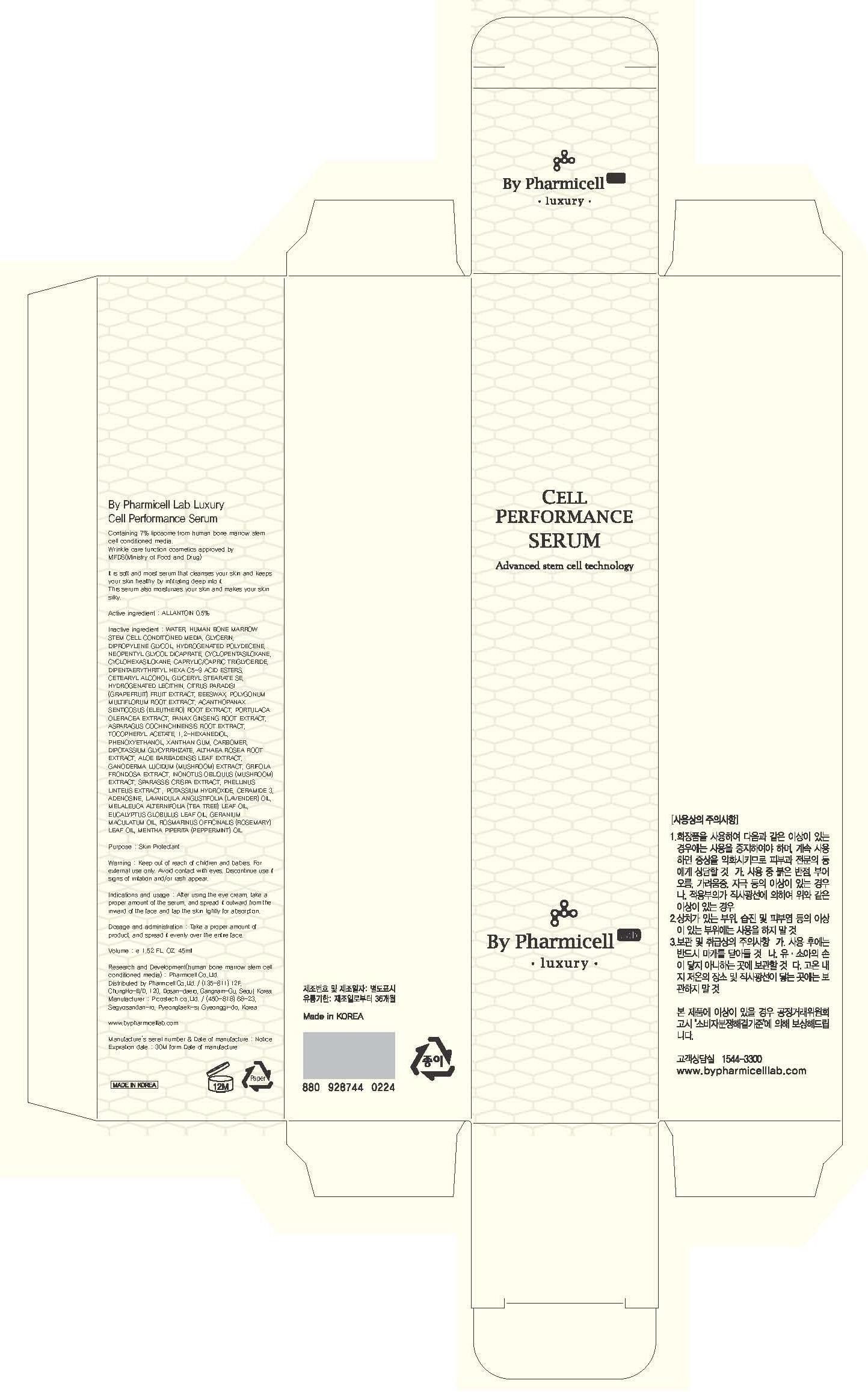 DRUG LABEL: By Pharmicell Lab Luxury Cell Performance Serum
NDC: 60949-080 | Form: CREAM
Manufacturer: Pharmicell Co., Ltd.
Category: otc | Type: HUMAN OTC DRUG LABEL
Date: 20130708

ACTIVE INGREDIENTS: ALLANTOIN 0.225 mg/45 mL
INACTIVE INGREDIENTS: WATER; GLYCERIN

ACTIVE INGREDIENT

Active ingredient : ALLANTOIN 0.5%

INACTIVE INGREDIENT

Inactive ingredient : WATER, HUMAN BONE MARROW STEM CELL CONDITIONED MEDIA, GLYCERIN, DIPROPYLENE GLYCOL, HYDROGENATED POLYDECENE, NEOPENTYL GLYCOL DICAPRATE, CYCLOPENTASILOXANE, CYCLOHEXASILOXANE, CAPRYLIC/CAPRIC TRIGLYCERIDE, DIPENTAERYTHRITYL HEXA C5-9 ACID ESTERS, CETEARYL ALCOHOL, GLYCERYL STEARATE SE, HYDROGENATED LECITHIN, CITRUS PARADISI (GRAPEFRUIT) FRUIT EXTRACT, BEESWAX, POLYGONUM MULTIFLORUM ROOT EXTRACT, ACANTHOPANAX SENTICOSUS (ELEUTHERO) ROOT EXTRACT, PORTULACA OLERACEA EXTRACT, PANAX GINSENG ROOT EXTRACT, ASPARAGUS COCHINCHINENSIS ROOT EXTRACT, TOCOPHERYL ACETATE, 1,2-HEXANEDIOL, PHENOXYETHANOL, XANTHAN GUM, CARBOMER, DIPOTASSIUM GLYCYRRHIZATE, ALTHAEA ROSEA ROOT EXTRACT, ALOE BARBADENSIS LEAF EXTRACT, GANODERMA LUCIDUM (MUSHROOM) EXTRACT, GRIFOLA FRONDOSA EXTRACT, INONOTUS OBLIQUUS (MUSHROOM) EXTRACT, SPARASSIS CRISPA EXTRACT, PHELLINUS LINTEUS EXTRACT , POTASSIUM HYDROXIDE, CERAMIDE 3, ADENOSINE, LAVANDULA ANGUSTIFOLIA (LAVENDER) OIL, MELALEUCA ALTERNIFOLIA (TEA TREE) LEAF OIL, EUCALYPTUS GLOBULUS LEAF OIL, GERANIUM MACULATUM OIL, ROSMARINUS OFFICINALIS (ROSEMARY) LEAF OIL, MENTHA PIPERITA (PEPPERMINT) OIL

PURPOSE

Purpose : Skin Protectant

WARNINGS

Warning : Keep out of reach of children and babies. For external use only. Avoid contact with eyes. Discontinue use if signs of irritation and/or rash appear.

Keep out of reach of children and babies.

Indications and usage : After using the eye cream, take a proper amount of the serum, and spread it outward from the inward of the face and tap the skin lightly for absorption.

Dosage and administration : Take a proper amount of product, and spread it evenly over the entire face.